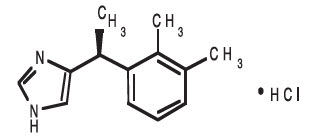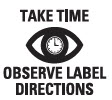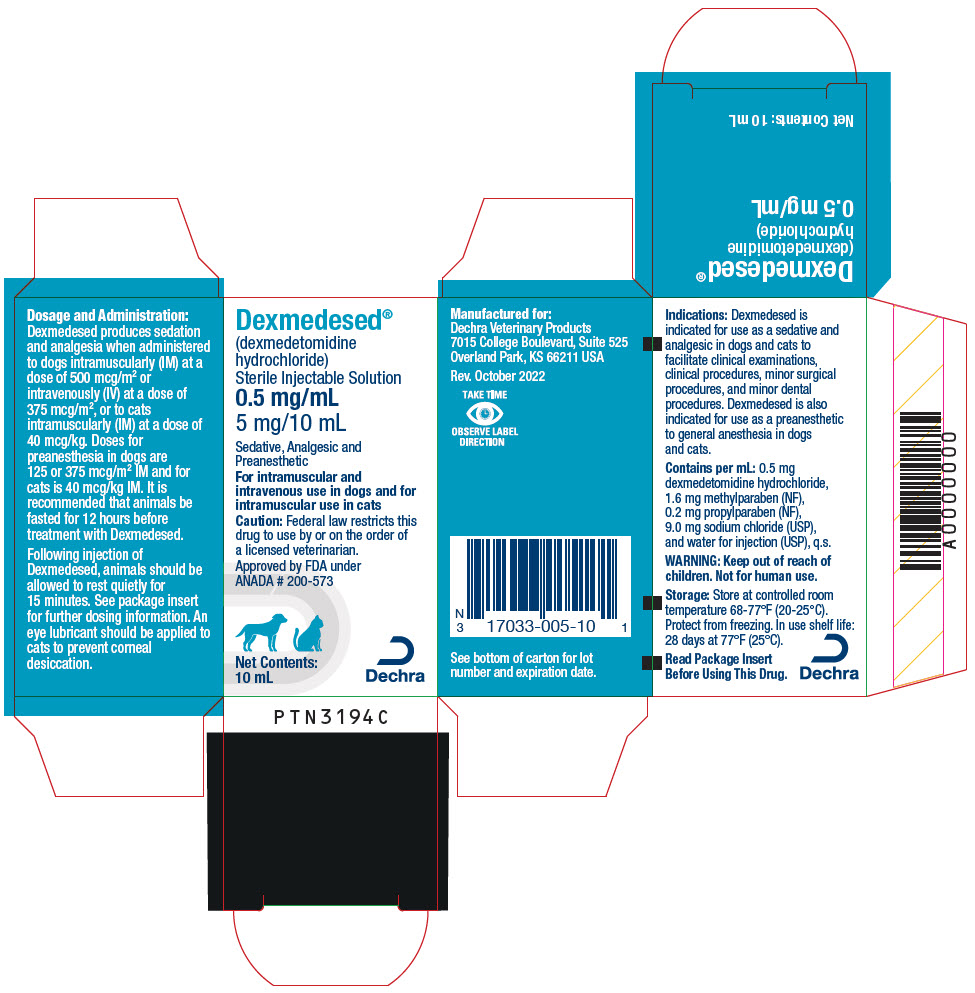 DRUG LABEL: Dexmedesed
NDC: 17033-005 | Form: INJECTION, SOLUTION
Manufacturer: Dechra Veterinary Products LLC
Category: animal | Type: PRESCRIPTION ANIMAL DRUG LABEL
Date: 20260217

ACTIVE INGREDIENTS: Dexmedetomidine Hydrochloride 0.5 mg/1 mL

Dexmedesed®
(dexmedetomidine hydrochloride)
Sterile Injectable Solution-0.5 mg/mL
For Intramuscular and Intravenous Use in Dogs
For Intramuscular Use in Cats
Sedative, Analgesic, Preanesthetic

CAUTION: Federal law restricts this drug to use by or on the order of a licensed veterinarian.

DESCRIPTION

DESCRIPTION: Dexmedesed (dexmedetomidine hydrochloride) is a synthetic alpha2-adrenoreceptor agonist with sedative and analgesic properties. The chemical name is (+)-4-[1-(2,3-dimethylphenyl) ethyl]-1H-imidazole monohydrochloride. It is a white, or almost white, crystalline, water soluble substance having a molecular weight of 236.7.

The molecular formula is C13 H16 N2 ∙ HCl and the structural formula is:

Each mL of Dexmedesed contains 0.5 mg dexmedetomidine hydrochloride, 1.6 mg methylparaben (NF), 0.2 mg propylparaben (NF), 9.0 mg sodium chloride (USP), and water for injection (USP), q.s.

VETERINARY INDICATIONS

INDICATIONS: Dexmedesed is indicated for use as a sedative and analgesic in dogs and cats to facilitate clinical examinations, clinical procedures, minor surgical procedures, and minor dental procedures. Dexmedesed is also indicated for use as a preanesthetic to general anesthesia in dogs and cats.

DOSAGE AND ADMINISTRATION:

Dogs: Sedation and Analgesia: 500 mcg/m^2 intramuscularly (IM) or 375 mcg/m^2 intravenously (IV).

Preanesthesia: 125 or 375 mcg/m^2 IM.

The choice of preanesthetic dose depends on the duration and severity of the procedure, as well as the anesthetic regime. The following two tables may be used to determine the correct dexmedetomidine dosage. Note that the mcg/kg dosage decreases as body weight increases. For example, dogs weighing 2 kg are dosed at 28.1 mcg/kg dexmedetomidine IV, compared to dogs weighing 80 kg that are dosed at 8.7 mcg/kg. Due to the small volume of administration, accurate dosing is not possible in dogs weighing less than 2 kg (4.4 lb).

Table 1: CANINE SEDATION/ANALGESIA DOSE TABLE: Intravenous (IV) and intramuscular (IM) dosing on the basis of body weight
Dexmedesed 0.5 mg/mL
Sedation/analgesia in dogs
Dog Weight |  | Dexmedetomidine 375 mcg/m^2 IV |  | Dexmedetomidine 500 mcg/m^2 IM
lbs | kg | mcg/kg | mL | mcg/kg | mL
4.4-7 | 2-3 | 28.1 | 0.12 | 40 | 0.15
7.1-9 | 3.1-4 | 25 | 0.15 | 35 | 0.2
9.1-11 | 4.1-5 | 23 | 0.2 | 30 | 0.3
11.1-22 | 5.1-10 | 19.6 | 0.29 | 25 | 0.4
22.1-29 | 10.1-13 | 16.8 | 0.38 | 23 | 0.5
29.1-33 | 13.1-15 | 15.7 | 0.44 | 21 | 0.6
33.1-44 | 15.1-20 | 14.6 | 0.51 | 20 | 0.7
44.1-55 | 20.1-25 | 13.4 | 0.6 | 18 | 0.8
55.1-66 | 25.1-30 | 12.6 | 0.69 | 17 | 0.9
66.1-73 | 30.1-33 | 12 | 0.75 | 16 | 1
73.1-81 | 33.1-37 | 11.6 | 0.81 | 15 | 1.1
81.1-99 | 37.1-45 | 11 | 0.9 | 14.5 | 1.2
99.1-110 | 45.1-50 | 10.5 | 0.99 | 14 | 1.3
110.1-121 | 50.1-55 | 10.1 | 1.06 | 13.5 | 1.4
121.1-132 | 55.1-60 | 9.8 | 1.13 | 13 | 1.5
132.1-143 | 60.1-65 | 9.5 | 1.19 | 12.8 | 1.6
143.1-154 | 65.1-70 | 9.3 | 1.26 | 12.5 | 1.7
154.1-176 | 70.1-80 | 9 | 1.35 | 12.3 | 1.8
>176 | >80 | 8.7 | 1.42 | 12 | 1.9

Table 2: CANINE PREANESTHESIA DOSE TABLE: Intramuscular (IM) dosing on the basis of body weight
Dexmedesed 0.5 mg/mL
Preanesthesia in dogs
Dog Weight |  | Dexmedetomidine 125 mcg/m^2 IM |  | Dexmedetomidine 375 mcg/m^2 IM
lbs | kg | mcg/kg | mL | mcg/kg | mL
4.4-7 | 2-3 | 9.4 | 0.04 | 28.1 | 0.12
7.1-9 | 3.1-4 | 8.3 | 0.05 | 25 | 0.15
9.1-11 | 4.1-5 | 7.7 | 0.07 | 23 | 0.2
11.1-22 | 5.1-10 | 6.5 | 0.1 | 19.6 | 0.29
22.1-29 | 10.1-13 | 5.6 | 0.13 | 16.8 | 0.38
29.1-33 | 13.1-15 | 5.2 | 0.15 | 15.7 | 0.44
33.1-44 | 15.1-20 | 4.9 | 0.17 | 14.6 | 0.51
44.1-55 | 20.1-25 | 4.5 | 0.2 | 13.4 | 0.6
55.1-66 | 25.1-30 | 4.2 | 0.23 | 12.6 | 0.69
66.1-73 | 30.1-33 | 4 | 0.25 | 12 | 0.75
73.1-81 | 33.1-37 | 3.9 | 0.27 | 11.6 | 0.81
81.1-99 | 37.1-45 | 3.7 | 0.3 | 11 | 0.9
99.1-110 | 45.1-50 | 3.5 | 0.33 | 10.5 | 0.99
110.1-121 | 50.1-55 | 3.4 | 0.35 | 10.1 | 1.06
121.1-132 | 55.1-60 | 3.3 | 0.38 | 9.8 | 1.13
132.1-143 | 60.1-65 | 3.2 | 0.4 | 9.5 | 1.19
143.1-154 | 65.1-70 | 3.1 | 0.42 | 9.3 | 1.26
154.1-176 | 70.1-80 | 3 | 0.45 | 9 | 1.35
>176 | >80 | 2.9 | 0.47 | 8.7 | 1.42

The use of dexmedetomidine as a preanesthetic markedly reduces anesthetic requirements in dogs. Injectable induction drug requirements for intubation will be reduced between 30% and 60%, depending on the choice of anesthetic and the dexmedetomidine preanesthetic dose. The concentration of inhalation maintenance anesthetic will be reduced between 40% and 60%, depending on the dose of dexmedetomidine. The anesthetic dose should always be titrated against the response of the patient. The choice of anesthetic is left to the discretion of the veterinarian.

Cats: Sedation, Analgesia and Preanesthesia: 40 mcg/kg intramuscularly (IM).

This dose can also be used as a preanesthetic and has been shown to markedly reduce anesthetic requirements in cats. Injectable anesthetic drug requirements for intubation were reduced up to 49%, depending on the choice of induction drug. The concentration of inhalation maintenance anesthetic was reduced between 35% and 44%, depending on the choice of induction drug. The anesthetic dose should always be titrated against the response of the patient.

The following table may be used to determine the correct dexmedetomidine dosage for cats based on body weight.

Table 3: FELINE DOSE TABLE: Intramuscular (IM) dosing on the basis of body weight in cats
Dexmedesed 0.5 mg/mL
Sedation/analgesia and preanesthesia in cats
Cat Weight |  | Dexmedetomidine 40 mcg/kg IM
lbs | kg | mcg/kg | mL
2-4 | 1-2 | 40 | 0.1
4.1-7 | 2.1-3 | 40 | 0.2
7.1-9 | 3.1-4 | 40 | 0.3
9.1-13 | 4.1-6 | 40 | 0.4
13.1-15 | 6.1-7 | 40 | 0.5
15.1-18 | 7.1-8 | 40 | 0.6
18.1-22 | 8.1-10 | 40 | 0.7

It is recommended that dogs and cats be fasted for 12 hours before treatment with Dexmedesed. An eye lubricant should be applied to cats to prevent corneal desiccation that may result from a reduction in the blink reflex. Following injection of Dexmedesed, the animal should be allowed to rest quietly for 15 minutes; sedation and analgesia occur within 5 to 15 minutes, with peak effects at 30 minutes after dexmedetomidine.

CONTRAINDICATIONS

CONTRAINDICATIONS: Do not use Dexmedesed in dogs or cats with cardiovascular disease, respiratory disorders, liver or kidney diseases, or in conditions of shock, severe debilitation, or stress due to extreme heat, cold or fatigue.

As with all alpha2-adrenoceptor agonists, the potential for isolated cases of hypersensitivity, including paradoxical response (excitation), exists.

WARNINGS:

Human safety: Not for human use. Keep out of reach of children.

Dexmedetomidine hydrochloride can be absorbed following direct exposure to skin, eyes, or mouth, and may cause irritation. In case of accidental eye exposure, flush with water for 15 minutes. In case of accidental skin exposure, wash with soap and water. Remove contaminated clothing.

Appropriate precautions should be taken while handling and using filled syringes. Accidental topical (including ocular) exposure, oral exposure, or exposure by injection could cause adverse reactions, including sedation, hypotension, and bradycardia. Seek medical attention immediately.

Users with cardiovascular disease (for example, hypertension or ischemic heart disease) should take special precautions to avoid any exposure to this product.

Caution should be exercised when handling sedated animals. Handling or any other sudden stimuli, including noise, may cause a defense reaction in an animal that appears to be heavily sedated.

The safety data sheet (SDS) contains more detailed occupational safety information. To report adverse reactions in users or to obtain a copy of the SDS for this product call (866) 933-2472.

Note to physician: This product contains an alpha2-adrenergic agonist.

Animal safety: Dexmedetomidine should not be administered in the presence of preexisting hypotension, hypoxia, or bradycardia. Due to the pronounced cardiovascular effects of dexmedetomidine, only clinically healthy dogs and cats (ASA classes I and II) should be treated. Animals should be frequently monitored for cardiovascular function and body temperature during sedation or anesthesia. Dexmedetomidine sedation is not recommended for cats with respiratory disease.

The use of dexmedetomidine as a preanesthetic in dogs and cats significantly reduces the amount of induction and maintenance anesthetic requirements. Careful patient monitoring during anesthetic induction and maintenance is necessary to avoid anesthetic overdose.

PRECAUTIONS

PRECAUTIONS: Apnea may occur with dexmedetomidine use. In the event of apnea, additional oxygen should be supplied. Administration of atipamezole to dogs is warranted when apnea is accompanied by bradycardia and cyanotic mucous membranes.

Adverse reaction reports for dexmedetomidine in cats include rare events of severe dyspnea and respiratory crackles diagnosed as acute pulmonary edema. Dyspnea due to the delayed onset of pulmonary edema could develop in rare instances up to three days after dexmedetomidine administration. Some of these acute and delayed pulmonary edema cases have resulted in death although this was not observed in the feline clinical field studies with dexmedetomidine.

In dogs, intramuscular atipamezole may be routinely used to rapidly reverse the effects of dexmedetomidine.

Since analgesic as well as sedative effects will be reversed, pain management may need to be addressed.

In cats, atipamezole has not been evaluated as a routine dexmedetomidine reversal agent. In cats, cases of dyspnea following atipamezole administration have been reported.

Dexmedetomidine has not been evaluated in the presence of other preanesthetics in cats. Although not observed in the feline field studies, death has been reported in cats receiving dexmedetomidine in conjunction with ketamine and butorphanol.

Analgesia resulting from preanesthetic dexmedetomidine may not provide adequate pain control during the postoperative or postprocedural period. Additional pain management should be addressed as needed.

Following administration of dexmedetomidine, a decrease in body temperature is likely to occur unless externally maintained.

Once established, hypothermia may persist longer than sedation and analgesia. To prevent hypothermia, treated animals should be kept warm and at a constant temperature during the procedure, and until full recovery.

Nervous or excited animals with high levels of endogenous catecholamines may exhibit a reduced pharmacological response to alpha2-adrenoceptor agonists like dexmedetomidine (ineffectiveness). In agitated animals, the onset of sedative/analgesic effects could be slowed, or the depth and duration of effects could be diminished or nonexistent. Therefore, allow dogs and cats to rest quietly for 10 to 15 minutes after injection. Repeat dosing has not been evaluated.

Administration of anticholinergic agents in dogs or cats at the same time or after dexmedetomidine could lead to adverse cardiovascular effects (secondary tachycardia, prolonged hypertension, and cardiac arrhythmias^1,2,3). However, an anticholinergic drug may be administered to dogs at least 10 minutes before dexmedetomidine for the prevention of the dexmedetomidine induced reduction in heart rate. Therefore, the routine use of anticholinergics simultaneously with, or after dexmedetomidine in dogs or cats, is not recommended (see ANIMAL SAFETY).

Spontaneous muscle contractions (twitching) can be expected in some dogs sedated with dexmedetomidine.

Dexmedetomidine has been evaluated only in fasted dogs; therefore, its effects on fed dogs (for example, the occurrence of vomiting) have not been characterized. In cats, there is a high frequency of vomition whether fed or fasted; therefore, fasting is recommended to reduce stomach contents.

Dexmedetomidine has not been evaluated in dogs younger than 16 weeks of age, in cats younger than 12 weeks of age, or in geriatric dogs and cats.

Dexmedetomidine has not been evaluated for use in breeding, pregnant, or lactating dogs or cats.

ADVERSE REACTIONS:

Canine sedation/analgesia field study: In the field study safety analysis, 106 dogs received dexmedetomidine and 107 received medetomidine. Dogs ranged from 16 weeks to 16 years of age, representing 49 breeds.

Table 4 shows the number of dogs displaying each clinical observation (some dogs experienced more than one adverse reaction).

The occurrence of ausculted unidentified arrhythmias (some at multiple time points) decreased following the administration of atipamezole.

Canine preanesthesia field study: The preanesthesia field study safety analysis included 192 dogs, between 5 months and 15 years of age, representing 43 breeds enrolled for elective procedures conducted under general anesthesia.

Table 5 shows the number of dogs within a treatment group that showed each clinical sign (dogs may have experienced more than one adverse reaction). Other clinical signs observed in dogs treated with dexmedetomidine include decreased respiratory rate and hypothermia.

Feline sedation/analgesia field study: The field study safety analysis included 242 cats (122 received dexmedetomidine; 120 received xylazine), 6 months to 17 years of age, and representing 19 breeds. Table 6 shows the number of cats reported with an adverse reaction (cats may have experienced more than one adverse reaction).

The most frequently observed adverse reaction was vomiting in both fasted and fed cats. Other infrequent clinical signs observed in cats treated with dexmedetomidine included fatigue, anorexia, cystitis, and peripheral vascular disorder.

One incidence of dyspnea was reported, 43 minutes after dexmedetomidine administration during an oral examination/dental procedure.

Prior to dexmedetomidine, the cat was free of clinical signs, but had a history of asthma and respiratory infection.

The cat responded successfully to treatment.

Feline preanesthesia field study: The field study safety analysis included 184 cats (116 received dexmedetomidine; 68 received saline), 12 weeks to 16 years of age, and representing 11 breeds. Table 7 shows the number of cats reported with an adverse reaction (cats may have experienced more than one adverse reaction).

One case of apnea was reported in a cat that received ketamine as the induction agent. This cat required artificial ventilation from the start of the procedure until 30 minutes into recovery when the cat began to breathe on its own. The cat recovered without further problems.

Table 4: Adverse reactions during the canine sedation/analgesia field study
 | Dexmedetomidine Total n=106 | Medetomidine Total n=107
Ausculted unidentified arrhythmias | 19 | 20
Severe bradycardia requiring treatment | 1 | 1
Apnea requiring treatment | 1 | 0
Slow onset of sedation (exceeding 30 minutes) | 1 | 1
Ineffectiveness (dog standing throughout the study) | 3 | 2
Severe hypothermia requiring treatment | 2 | 0
Prolonged recovery | 1 | 4

Table 5: Adverse reactions during the canine preanesthesia field study
 | Treatment Groups
Induction Anesthetic: | Propofol |  |  | Barbiturate
Preanesthetic dose: | 0 mcg/m^2 n=32 | 125 mcg/m^2 n=32 | 375 mcg/m^2 n=32 | 0 mcg/m^2 n=32 | 125 mcg/m^2 n=32 | 375 mcg/m^2 n=32
Emesis | 4 | 7 | 4 | 2 | 3 | 6
Ventricular premature contractions | 0 | 2 | 0 | 4 | 1 | 0
Diarrhea | 1 | 0 | 0 | 3 | 1 | 1
Self trauma | 0 | 2 | 1 | 2 | 1 | 0
Severe bradycardia | 0 | 0 | 1 | 0 | 0 | 1
Tachycardia | 0 | 0 | 0 | 1 | 1 | 0
Urinary incontinence | 0 | 0 | 0 | 0 | 0 | 1

Table 6: Adverse reactions during the feline sedation/analgesia field study
 | Dexmedetomidine n=122 | Xylazine n=120
Vomiting | 70 | 82
Urinary incontinence | 6 | 11
Hypersalivation | 4 | 5
Involuntary defecation | 4 | 1
Hypothermia | 2 | 1
Diarrhea | 2 | 0
Arrhythmia | 1 | 2
Corneal ulcer | 1 | 0
Cyanosis | 1 | 0
Dyspnea | 1 | 0

Table 7: Adverse reactions during the feline preanesthesia field study
Induction Anesthetic: | Ketamine |  | Propofol
Preanesthetic | Saline n=37 | Dexmedetomidine n=64 | Saline n=31 | Dexmedetomidine n=52
Emesis | 2 | 20 | 1 | 12
Pale mucous membranes |  | 11 |  | 9
Decreased body temperature |  | 4
Retching |  | 1 | 1 | 3
Heart murmur |  |  |  | 2
Loose stool |  | 2
Corneal injury | 1
Apnea |  | 1
Behavioral change |  |  | 1
Fluid in endotracheal tube |  |  | 1

POST APPROVAL EXPERIENCE: The following adverse events were obtained from post-approval adverse drug events reported for dexmedetomidine hydrochloride sterile injectable solution from 2007-2009. Not all adverse reactions are reported. Some adverse reactions occurred when dexmedetomidine hydrochloride was used alone for sedation; most occurred when dexmedetomidine hydrochloride was used in the presence of anesthetics and/or other preanesthetics.

It is not always possible to reliably estimate the frequency of an adverse event or to establish a causal relationship to the drug, especially when multiple drugs are administered.

The following reported adverse events are listed in decreasing order of frequency:

Dogs: ineffective for sedation, death, bradycardia, cardiac arrest, apnea, convulsions, vomiting, prolonged sedation, elevated temperature, and delayed sedation.

Cats: ineffective for sedation, death, cardiac arrest, vomiting, apnea, prolonged sedation, hypersalivation, hypothermia, bradycardia, cyanotic mucous membranes, sedation too brief, and dyspnea.

To report suspected adverse drug events, for technical assistance, or to obtain a copy of the Safety Data Sheet, contact Dechra Veterinary Products at (866) 933-2472.

For additional information about adverse drug experience reporting for animal drugs, contact FDA at 1-888-FDA-VETS or http://www.fda.gov/reportanimalae

INFORMATION FOR OWNERS/CAREGIVERS

INFORMATION FOR OWNERS: Owners should notify their veterinarian immediately if their cat experiences difficulty breathing due to the rare possibility of delayed onset of pulmonary edema which has been associated with administration of alpha2-adrenergic agonists in cats.

CLINICAL PHARMACOLOGY

CLINICAL PHARMACOLOGY: Dexmedetomidine is a potent non-narcotic alpha2-adrenoceptor agonist which produces sedation and analgesia. These effects are dose dependent in depth and duration. Blood pressure is initially increased due to peripheral vasoconstriction, subsequently dropping to normal or slightly below normal levels. Vasoconstriction may cause mucous membranes to appear pale or mildly cyanotic. This initial vasopressor response is accompanied by a compensatory marked decrease in heart rate mediated by a vagal baroreceptor. The peripheral pulse may feel weak and a transient change in the conductivity of the cardiac muscle may occur, as evidenced by first and second degree atrioventricular blocks. Other arrhythmias may occur. Dexmedetomidine also decreases the respiratory rate and decreases body temperature. The magnitude and duration of the decrease in body temperature is dose dependent. Dexmedetomidine causes depression of gastrointestinal motility due to decrease in smooth muscle activity, increases in blood glucose levels due to inhibition of insulin release, and increases in production of urine. Spontaneous muscle contractions (twitching) can be expected in some dogs sedated with dexmedetomidine. Vomiting in cats has been associated with alpha2-adrenergic agonist central stimulation of the brain^4.

EFFECTIVENESS:

Canine sedation/analgesia field study: Dexmedetomidine was evaluated in a masked, controlled, multi-site field study, using parallel treatment groups. Effectiveness was evaluated in 200 (of 213) healthy client-owned dogs, ranging in age between 16 weeks and 16 years of age, and in size between 4.8 lbs and 141 lbs (2.2 kg and 64 kg). Dogs admitted to veterinary clinics for various procedures requiring sedation and/or analgesia received either dexmedetomidine or medetomidine once, by IV or IM injection. Procedures included dental care, radiography, minor skin tumor removal, and treatment of otitis.

Sedation and analgesia occurred within 5 minutes after IV dexmedetomidine, and within 15 minutes after IM dexmedetomidine, with peak effects approximately at 15 or 30 minutes, respectively. Effects waned by approximately two hours after IV administration, and by three hours using the IM route. Dexmedetomidine and medetomidine showed comparable clinical effects.

Cardiac rhythms were evaluated by auscultation. Bradycardia occurred within 5 to 15 minutes after IV dexmedetomidine or medetomidine, and within 15 to 30 minutes after either drug given IM. Sixty-four dexmedetomidine-treated dogs and 50 medetomidine-treated dogs were observed with bradycardia.

Adverse reactions during the field study included ausculted unidentified arrhythmias, apnea, hypothermia, and ineffectiveness (see ADVERSE REACTIONS).

Eleven dogs received concomitant medication during the field study, including amoxicillin, cephalexin, triamcinolone, methyl-prednisolone acetate, neomycin, nystatin, thiostrepton, acepromazine, atropine, and atipamezole.

The results of this field study demonstrate that dexmedetomidine produces satisfactory levels of sedation and analgesia for clinical examinations and procedures, minor surgical procedures, and minor dental procedures.

Canine preanesthesia field study: The use of dexmedetomidine as a preanesthetic was evaluated in a controlled, multi-site field study, using parallel treatment groups. Effectiveness was evaluated in 192 healthy, client-owned dogs, between 5 months and 15 years of age, weighing 4 to 196 lbs (2 kg to 89 kg). Dogs received IM dexmedetomidine or saline as a preanesthetic to general anesthesia.

All dogs were induced by an injectable anesthetic; half of the dogs were maintained with an inhalation anesthetic. Procedures included orchiectomy, ovariohysterectomy, skin surgery, radiography, physical examination, dental procedures, ear cleaning, anal sac treatment, and grooming.

Compared to saline controls, dexmedetomidine IM reduced induction drug requirements by 30-36% (at 125 mcg/m^2) and by 38-61% (at 375 mcg/m^2). Inhalation anesthetic requirements were 40-60% less for dexmedetomidine-preanesthetized dogs. The number of dogs with clinical signs of pain was less for at least 30 minutes after the procedure in dogs treated with 375 mcg/m^2 dexmedetomidine, compared to saline controls.

Recovery times were dose dependent, averaging 15-32 minutes to extubation and 71-131 minutes to standing recovery (longer times correspond to higher dexmedetomidine dose). Recovery times also depended on the induction anesthetic. Recovery times following barbiturate induction were longer (30 minutes to extubation and 118 minutes to standing), compared to dogs induced with propofol (23 minutes to extubation and 84 minutes to standing).

Cardiac arrhythmias were monitored by ECG. Dexmedetomidine-treated dogs were more frequently observed with at least one incidence of arrhythmia compared to saline controls. The most commonly observed arrhythmias were bradycardia, 1st and 2nd degree AV block, and sinus arrest. Other less frequently observed arrhythmias included ventricular premature complexes (VPCs), supraventricular premature complexes, 3rd degree AV block, and sinus pause.

Adverse events included bradycardia, tachycardia, VPCs, vomiting, diarrhea, urinary incontinence, and self trauma (see ADVERSE REACTIONS). The results of the preanesthesia field study demonstrate that dexmedetomidine provided anesthetic dose-sparing, sedation, and analgesia during procedures conducted under general anesthesia.

Feline sedation/analgesia field study: Dexmedetomidine hydrochloride was evaluated in a masked, controlled, multiple site field study, using parallel treatment groups. Effectiveness was evaluated in 242 client-owned cats, ranging in age between 6 months and 17 years, and in size between 2.3 and 9.6 kg (5 and 21 lbs). Cats admitted to veterinary clinics for various procedures requiring restraint, sedation, and/or analgesia were randomized to treatment group and given dexmedetomidine (122 cats) or xylazine (120 cats) once by IM injection. Procedures performed using dexmedetomidine included dental care, radiography, minor superficial surgery, otitis treatment, blood or urine sample collection, tattooing, microchip placement, and grooming.

Sedation and analgesia occurred within 5 to 15 minutes and peak effects were observed 30 minutes after dexmedetomidine.

The procedure was easily performed in 91% of cats beginning 30 minutes after dexmedetomidine. Sedative and analgesic effects waned by three hours after dexmedetomidine.

Signs of sedation were deeper for cats receiving dexmedetomidine compared to those receiving xylazine. No clinically relevant differences were observed between dexmedetomidine and xylazine with respect to analgesia or physiological variables. Heart rate, respiratory rate, and rectal temperature decreased. Bradycardia was observed within 5 to 15 minutes and heart rates of ≤70 beats/minute were seen in 18% of cats. The most commonly observed arrhythmias assessed with ECG were atrioventricular dissociation and escape rhythms, followed by a few incidences of premature complexes and one incidence of atrioventricular block. Oxygen saturation, mucous membrane color, capillary refill time, pulse character, respiratory depth and pattern, and response of the animal to injection were clinically satisfactory. All cats recovered from changes induced by dexmedetomidine.

Ninety-seven adverse events were reported after dexmedetomidine. The most frequently reported adverse reactions included vomiting (70), urinary incontinence (6), hypersalivation (4), involuntary defecation (4), hypothermia (2), and diarrhea (2) (see ADVERSE REACTIONS). The results of this field study demonstrate that dexmedetomidine produces satisfactory levels of sedation and analgesia for clinical examinations and procedures, minor surgical procedures, and minor dental procedures.

Feline preanesthesia field study: The use of dexmedetomidine as a preanesthetic was evaluated in a masked, controlled, multi-site field study, using parallel treatment groups. Effectiveness was evaluated in 182 healthy, client-owned cats, between 12 weeks and 16 years of age, weighing 2.10 to 18.8 lbs (0.9 kg to 8.5 kg). Preanesthetic/induction drug regimens included saline/ketamine, dexmedetomidine/ketamine, saline/propofol, and dexmedetomidine/propofol. All cats were intubated prior to the procedure. Inhalant anesthesia (isoflurane) was added during longer procedures (>15 minutes) and could be added during shorter procedures if the veterinarian deemed it necessary. Procedures included ovariohysterectomy, orchiectomy, onychectomy, and dental cleaning.

Dexmedetomidine IM administered at 40 mcg/kg prior to induction with ketamine resulted in a significantly higher proportion of cats that were successfully intubated compared to saline (success rates of 89.5% and 10.7%, respectively).

Cats preanesthetized with dexmedetomidine IM required 48.9% less propofol for successful intubation compared to cats that received saline. Inhalant anesthetic requirements were 35-44% less for dexmedetomidine preanesthetized cats. Recovery times following ketamine and propofol induction averaged 36 and 38 minutes to extubation and 161 and 131 minutes to standing, respectively for dexmedetomidine-treated groups.

Dexmedetomidine (followed by ketamine or propofol) resulted in the following ECG abnormalities (in decreasing order of frequency): sinus bradycardia, sinus arrhythmia, 1st degree atrioventricular (AV) block, long QT interval, sinus pauses, ventricular premature depolarizations, 2nd degree AV block, escape beats/rhythms, and supraventricular premature depolarizations. Dexmedetomidine-treated cats had a lower mean heart rate, respiratory rate, and body temperature compared to saline controls continuing through the recovery period.

Sixty-six adverse events were reported after dexmedetomidine. The most frequently reported adverse events were: vomiting (32), pale mucous membranes (20), decreased body temperature (4), and retching (4) (see ADVERSE REACTIONS).

ANIMAL SAFETY:

Canine safety study: In the multiple dose safety study, dexmedetomidine was administered at 0, 1, 3 or 5 times (×) the recommended IV and IM doses on 3 consecutive days to a total of 36 healthy, young beagles. Two additional groups were given a 3× dose of dexmedetomidine (IV or IM) followed by three 1× doses of the reversal agent, atipamezole, every 30 minutes. This was repeated for a total of 3 days. No deaths occurred during the study.

1× dose group: At the recommended dose, sedation lasted less than 3 hours. During sedation, muscle twitches occurred intermittently, and decreases in temperature, respiratory rate and heart rate were observed in all animals. A slow pupil response to light was seen transiently about 15 minutes after dosing in one of twelve dogs. Second degree atrioventricular (AV) blocks were observed in one of twelve dogs.

3× dose group: At 3 times the recommended dose, the duration of sedation was between two and eight hours. During sedation, muscle twitches occurred, and temperature, respiratory rate, and heart rate decreased in all dogs. The pupillary light reflex was transiently decreased for up to 90 minutes in four of twelve dogs. Vomiting was seen in two of twelve dogs. One dog experienced first and second degree AV blocks; second degree AV block was observed in three of twelve dogs. Elevated concentrations of alanine aminotransferase (ALT) were observed in one dog, without histological changes to the liver.

5× dose group: At 5 times the recommended dose, the duration of sedation was between four and eight hours. Muscle twitches, decreases in temperature, respiratory rates, and heart rates were seen in all dogs. No pupil response was noted in six of twelve dogs (IV) for up to 1.5 hours; decreased transient pupillary light reflex was seen for up to 60 minutes in two of twelve dogs (IM). Vomiting was seen in one of twelve dogs.

First and second degree AV blocks were observed in one of twelve dogs. Elevated concentrations of ALT were observed in 3 of 12 dogs, without histological changes to the liver.

Dexmedetomidine demonstrated dose dependent effects related to its pharmacology when administered IV or IM to healthy dogs at doses up to five times the recommended dose.

Canine safety study with an anticholinergic: In another laboratory safety study, one of three doses of an IM anticholinergic drug or saline was administered 10 minutes before, at the same time, or 15 minutes after 500 mcg/m^2 IM dexmedetomidine. The anticholinergic drug was given for the prevention or treatment of dexmedetomidine-induced reduction in heart rate. In a crossover design, 18 dogs were used in a total of 72 trials, to evaluate the safety of dexmedetomidine used with an anticholinergic drug.

Dogs were instrumented for the accumulation of continuous ECG data. The following arrhythmias were recorded during the study (some dogs experienced more than one arrhythmia).

Table 8: Arrhythmias recorded during the canine laboratory safety study [Table does not relate arrhythmias to the presence or absence of anticholinergic]
Type of arrhythmia | Number of dogs (of 18)
Second degree AV block | 18
Supraventricular tachycardia (SVT) or SVPCs | 16
Ventricular escape beats | 16
Ventricular premature contractions | 14
Third degree AV block | 6
Idioventricular rhythm | 1
Paroxysmal VT | 1
Ventricular bigeminy; SVPCs; pulse alternans | 1
Junctional escape beat | 1

The occurrence of arrhythmias was not related to the presence or absence of the anticholinergic drug. Arrhythmias were transient (although frequent over time in some dogs), returning toward baseline levels within 55 minutes after dexmedetomidine.

No dogs required treatment related to these arrhythmias, and none of these arrhythmias persisted or adversely affected the overall clinical status of any dog in the study.

Dexmedetomidine without anticholinergic: Without the anticholinergic drug, and in addition to arrhythmias, dexmedetomidine produced clinically relevant sedation accompanied by a statistically significant reduction in heart rate, respiratory rate, cardiac output, pulmonary arterial temperature, and mixed venous oxygen tension. A statistically significant increase in arterial blood pressure, pulmonary capillary wedge pressure, central venous pressure, and systemic vascular resistance was noted. No dogs experienced hypotension.

Dexmedetomidine tended to increase pulmonary vascular resistance. Dexmedetomidine alone had no statistically significant effect on mean pulmonary arterial pressure, arterial pH, arterial carbon dioxide tension, and arterial oxygen tension.

Dexmedetomidine plus anticholinergic: Either of the two higher anticholinergic doses was effective in the prevention or treatment of the dexmedetomidine-induced reduction in heart rate. Anticholinergic (higher doses) given after dexmedetomidine caused marked increases in the occurrence of various cardiac arrhythmias, especially second degree AV block. When the higher doses of anticholinergic drug were given at the same time or 15 minutes after dexmedetomidine, large increases in heart rate (p<0.01) and blood pressure (p<0.05) were seen. Increases were dose related; the highest anticholinergic dose elicited more frequent arrhythmias and larger increases in heart rate and blood pressure.

In conclusion, moderate doses of anticholinergic drug given prior to dexmedetomidine performed best for the prevention of dexmedetomidine-induced reduction of heart rate in dogs. The routine use of anticholinergics given simultaneously with, or after dexmedetomidine, is not recommended.

Feline safety study: In a multiple dose safety study, dexmedetomidine hydrochloride, was administered intramuscularly (IM) at 1×, 3×, and 5× (40, 120, and 200 mcg/kg) the recommended dose of 40 mcg/kg on 3 consecutive days to healthy cats, 6 to 8 months old. A control group received the product vehicle as a placebo (0×). No mortality was observed. The depth and duration of sedation was dose dependent, lasting approximately 2 hours in the 1× group, 2 to 4 hours in the 3× group, and greater than 8 hours in the 5× group. The lowest recorded individual heart rate was 60 beats/minute and occurred in the 5× dose group (2 cats). Cardiac arrhythmias characterized by isolated junctional escape complexes with episodes of junctional escape rhythm were observed during periods of low heart rate or following sinus pauses in all dexmedetomidine dose groups. In most cases the arrhythmia was no longer observed after 1 to 2 hours. Atrioventricular block was not observed. Incidences of arrhythmias were not related to dose; however, more cats were affected by cardiac arrhythmias on the third day of treatment, compared to the first two days of the study. The decrease in respiratory rate, but not the duration, was dose dependent. The rectal temperature decreased in all dexmedetomidine-treated groups, with the lowest temperatures in the 5× group at 8 hours on all three days. Two cats vomited (40 and 120 mcg/kg). Corneal opacity was noted in all dexmedetomidine-dose groups, was transient, related to dose and duration of sedation, and was attributed to lack of lubrication with decreased blinking during sedation. Hematology and blood chemistry were unaffected by treatment. Injection site tolerance was good, with mild inflammatory lesions representative of the IM injection procedure. Gross and histological examination of all other tissues did not reveal any abnormalities related to dexmedetomidine hydrochloride administration.

Dexmedetomidine demonstrated dose dependent effects related to its pharmacology when administered IM to healthy cats at doses up to five times the recommended dose.

Feline acute tolerance study: IM dexmedetomidine hydrochloride was administered once at 10× (400 mcg/kg) the recommended dose of 40 mcg/kg to 3 female and 3 male 7 month old cats. No mortality was observed. Sedation was observed within 15 minutes of dosing and lasted for at least 4 hours with full recovery noted between 8 and 24 hours after dosing. Transient observations of corneal dehydration and opacity, miosis, pale skin and gingiva, salivation, and watery ocular discharge were observed in some animals. Vomiting was observed 7 to 11 hours after dosing in all but one animal. Decreases in heart rate accompanied by prolonged PQ and QT intervals were most pronounced 2 to 4 hours after dosing.

No atrioventricular (AV) blocks or escape rhythms were noted. In one cat, incidental and reversible premature junctional complexes were seen at 1 and 2 hours after dosing which were considered secondary to bradycardia. Slightly lower respiratory rate and reduced rectal temperature were observed 4 to 8 hours after dosing. Observations had returned to normal by 24 hours after dosing. Mild inflammatory lesions observed histologically at the injection site were representative of the IM injection procedure. No treatment related changes were observed in hematology. Mild elevations in some clinical ALT, AST, and CK, were observed 24 hours after dosing, with a trend towards recovery by 48 hours. Total protein, albumin and globulin levels were slightly lowered in one cat 48 hours after dosing.

STORAGE AND HANDLING

STORAGE INFORMATION: Store at controlled room temperature 68-77°F (20-25°C). Protect from freezing. In use shelf life: 28 days at 77°F (25°C).

HOW SUPPLIED

HOW SUPPLIED: Dexmedesed (dexmedetomidine hydrochloride) is supplied in 10-mL, multidose vials containing 0.5 mg of dexmedetomidine hydrochloride per mL.

Approved by FDA under ANADA # 200-573

REFERENCES:

(1) Ko JCH, Fox SMF, Mandsager RE. Effects of preemptive atropine administration on incidence of medetomidine-induced bradycardia in dogs. J Am Vet Med Assoc 2001; 218:52-58.
(2) Alibhai HIK, Clarke KW, Lee YH, et al. Cardiopulmonary effects of combinations of medetomidine hydrochloride and atropine sulphate in dogs. Vet Rec 1996; 138:11-13.
(3) Short, CE. Effects of anticholinergic treatment on the cardiac and respiratory systems in dogs sedated with medetomidine. Vet Rec 1991; 129:310-313.
(4) Hikasa Y, Akiba T, Iino Y et al. Central alpha-adrenoceptor subtypes involved in the emetic pathway in cats. Eur J Pharmacol 1992; 229:241-251

Manufactured for:
Dechra Veterinary Products
7015 College Boulevard, Suite 525
Overland Park, KS 66211 USA

Dexmedesed® is a registered trademark of Dechra Veterinary Products, LLC.
©2022. Dechra Veterinary Products, LLC.

PTN3195C

Rev. April 2022

PRINCIPAL DISPLAY PANEL - 5 mg/10 mL Vial Carton

Dexmedesed®
(dexmedetomidine hydrochloride)
Sterile Injectable Solution

0.5 mg/mL
5 mg/10 mL

Sedative, Analgesic and Preanesthetic

For intramuscular and intravenous use in dogs and for intramuscular use in cats

Caution: Federal law restricts this drug to use by or on the order of a licensed veterinarian.

Approved by FDA under ANADA # 200-573

Net Contents: 10 mL

Dechra